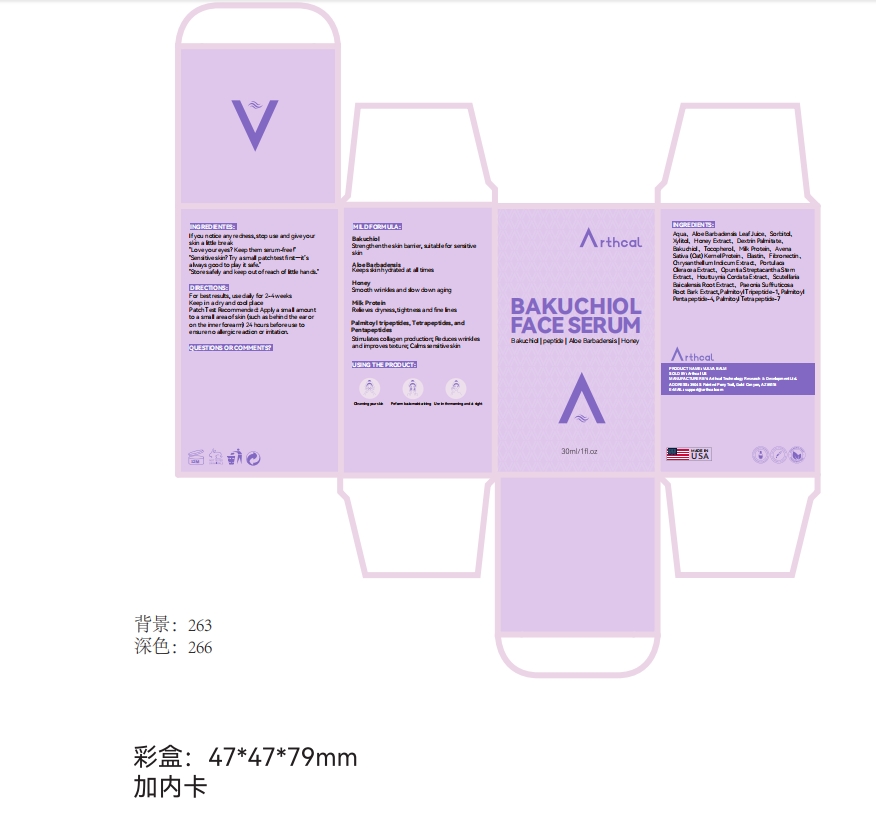 DRUG LABEL: Arthcal BAKUCHIOL FACE SERUM
NDC: 85212-0022 | Form: LIQUID
Manufacturer: Beijing JUNGE Technology Co., Ltd.
Category: otc | Type: HUMAN OTC DRUG LABEL
Date: 20250303

ACTIVE INGREDIENTS: BAKUCHIOL 1 g/100 mL
INACTIVE INGREDIENTS: SORBITOL 5 mL/100 mL; GLYCERIN 3 mL/100 mL; FIBRONECTIN 0.5 mL/100 mL; ALOE BARBADENSIS LEAF JUICE 5 mL/100 mL; PORTULACA OLERACEA WHOLE 0.2 mL/100 mL; MILK PROTEIN 1 mL/100 mL; PAEONIA SUFFRUTICOSA ROOT 0.1 mL/100 mL; TOCOPHEROL 1 mL/100 mL; HONEY 2 mL/100 mL; CHRYSANTHELLUM INDICUM FLOWER 0.2 mL/100 mL; HOUTTUYNIA CORDATA WHOLE 0.1 mL/100 mL; AQUA 74.7 mL/100 mL; XYLITOL 3 mL/100 mL; DEXTRIN PALMITATE (CORN; 20000 MW) 2 mL/100 mL; SCUTELLARIA BAICALENSIS ROOT 0.1 mL/100 mL; ELASTIN 0.5 mL/100 mL; SODIUM HYALURONATE 0.5 mL/100 mL; OPUNTIA STREPTACANTHA STEM 0.1 mL/100 mL

INSTRUCTIONS FOR USE

For besl results, use daily for 2 -4 weeks

Keep in a dry and cool place

Palch Test Recormended: Apply a small amount to a small area of skin (such as behind the ear or on the inner forearm) 2' hours belore use to ensure no allergic reaclon or irrilalon.

DOSAGE AND ADMINISTRATION

30ml(1fl.oz)

INDICATIONS AND USAGE

STEP1 :Cleansing your skin
STEP2 :Perform basic moisturizing
STEP3 :Use in the morning and at night

PURPOSE

Unlocking Anti-Aging Secrets

INACTIVE INGREDIENT

AQUA
ALOE BARBADENSIS LEAF JUICE
SORBITOL
XYLITOL
GLYCERIN
HONEY EXTRACT
DEXTRIN PALMITATE
TOCOPHEROL
MILK PROTEIN
ELASTIN
FIBRONECTIN
SODIUM HYALURONATE
CHRYSANTHELLUM INDICUM EXTRACT
PORTULACA OLERACEA EXTRACT
OPUNTIA STREPTACANTHA STEM EXTRACT
HOUTTUYNIA CORDATA EXTRACT
SCUTELLARIA BAICALENSIS ROOT EXTRACT
PAEONIA SUFFRUTICOSA ROOT EXTRACT

Keep Out of Reach of Children.

WARNINGS

For External Use Only.
Avoid Direct Contact with Eyes.
If the product gets into your eyes, rinse immediately with plenty of water.
Discontinue Use if Irritation Occurs: If redness, itching, or irritation develops, stop use and consult a dermatologist.
Do Not Apply on Broken or Irritated Skin.